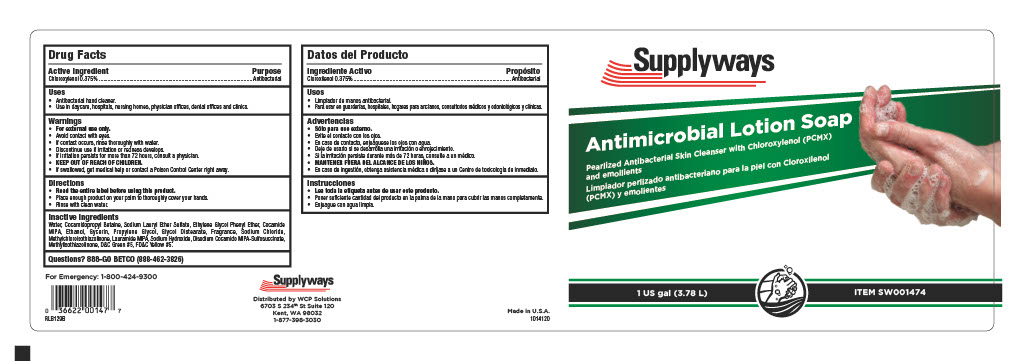 DRUG LABEL: Skin Cleanser
NDC: 72528-141 | Form: SOAP
Manufacturer: West Coast Paper Company
Category: otc | Type: HUMAN OTC DRUG LABEL
Date: 20241114

ACTIVE INGREDIENTS: CHLOROXYLENOL 3.75 mg/1 mL
INACTIVE INGREDIENTS: LINALOOL, (+/-)-; .BETA.-CITRONELLOL, (+/-)-; LAURIC ISOPROPANOLAMIDE; PHENYLETHYL ALCOHOL; COCAMIDOPROPYLAMINE OXIDE; HEXAHYDRO-4,7-METHANOINDEN-6-YL PROPIONATE; CALCIUM SILICATE; SODIUM ALUMINIUM SILICATE; 2,6-DIMETHYL-5-HEPTENAL; .GAMMA.-UNDECALACTONE; 2-TERT-BUTYLCYCLOHEXYL ACETATE; 1-(2,3,8,8-TETRAMETHYL-1,2,3,4,5,6,7,8-OCTAHYDRONAPHTHALEN-2-YL)ETHANONE; ETHYLENE BRASSYLATE; BENZYL ACETATE; 4-ACETOXY-3-PENTYLTETRAHYDROPYRAN; .ALPHA.-HEXYLCINNAMALDEHYDE; SODIUM HYDROXIDE; COCAMIDOPROPYL BETAINE; GLYCOL DISTEARATE; SODIUM CHLORIDE; SODIUM LAURETH SULFATE; WATER; PHENOXYETHANOL; D&C GREEN NO. 5; SUCCINIC ACID; PROPYLENE GLYCOL; FD&C YELLOW NO. 5; ETHYLENE OXIDE; BENZYL SALICYLATE; HEXYL SALICYLATE; VERDYL ACETATE; .ALPHA.-AMYLCINNAMALDEHYDE; DIHYDROMYRCENOL; SODIUM CARBONATE; 2-ISOBUTYL-4-METHYLTETRAHYDROPYRAN-4-OL; SODIUM LAURYL SULFATE; TRIBASIC CALCIUM PHOSPHATE; SODIUM BENZOATE

Supplyways Antimicrobial Lotion Soap

Active Ingredient

Chloroxylenol 0.375%

Uses

Antibacterial hand cleaner

Use in daycare, hospitals, nursing homes, physician offices, dental offices and clinics

Warnings

For external use only

Avoid contact with eyes

If contact occurs, risne thoroghly with water

Discontinue use if irritation or redness develops

If irritation persists for more than 72 hours, consult a physician

KEEP OUT OF REACH OF CHILDREN

If swallowed, get medical help or contact a Poison COntrol Center right away

Directions

Read the entire label before using this product

Place enough product on your palm to thoroughly cover your hands

Rinse with clean water

Inactive Ingredients

Water, Cocamidopropyl Betaine, Sodium Lauryl Ether Sulfate, Ethylene Glycol Phenyl Ether, Cocamide
MIPA, Ethanol, Gycerin, Propylene Glycol, Glycol Distearate, Fragrance, Sodium Chloride,
Methylchloroisothiazolinone, Lauramide MIPA, Sodium Hydroxide, Disodium Cocamido MIPA-Sulfosuccinate,
Methylisothiazolinone, D&C Green #5, FD&C Yellow #5.

Purpose

Antibacterial

KEEP OUT OF REACH OF CHILDREN

Recent major changes

Directions